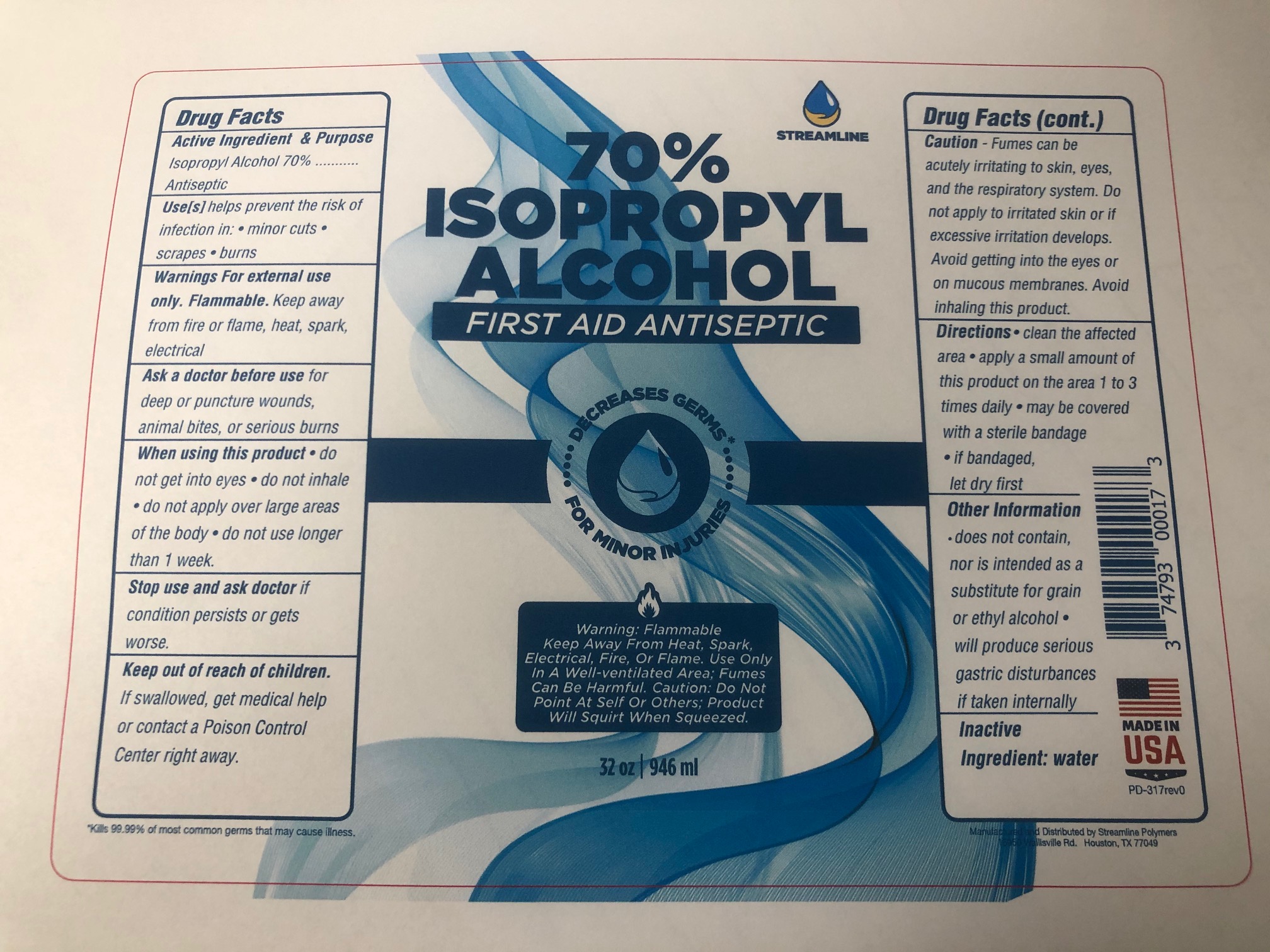 DRUG LABEL: 70% Isopropyl Alcohol
NDC: 74793-0008 | Form: LIQUID
Manufacturer: Streamline Polymers LLC
Category: otc | Type: HUMAN OTC DRUG LABEL
Date: 20220113

ACTIVE INGREDIENTS: ISOPROPYL ALCOHOL 70 mL/100 mL
INACTIVE INGREDIENTS: WATER 30 mL/100 mL

70% Isopropyl Alcohol Antiseptic

This is a first aid antiseptic. The product is manufactured using only the following United States Pharmacopoeia (USP) grade ingredients.

1. Isopropyl Alcohol (70%, v/v) in an aqueous solution.
2. Sterile distilled water or boiled cold water.

The firm does not add other active or inactive ingredients.

Active Ingredient(s)

Isopropyl Alcohol 70% v/v. Purpose: Antiseptic

Purpose

Antiseptic

Use

Use(s) helps prevent the risk of infection in: minor cuts, scrapes, burns

Warnings

For external use only. Flammable. Keep away from fire or flame, heat, spark, electrical

When using this product keep out of eyes, do not inhale, do not apply over large areas of the body, do not use longer than 1 week.
Stop use and ask a doctor if condition persists or get worse.
Keep out of reach of children. If swallowed, get medical help or contact a Poison Control Center right away.

Stop use and ask a doctor if irritation or rash occurs. These may be signs of a serious condition.

Keep out of reach of children. If swallowed, get medical help or contact a Poison Control Center right away.

Directions

clean the affected area, apply a small amount of this product on the area 1 to 3 times daily, may be covered with a sterile bandage, if bandaged, let dry first

Other information

- does not contain nor is intended as a substitute for grain or ethyl alcohol
- will produce serious gastric disturbances if taken internally

Inactive ingredients

purified water USP

Package Label - Principal Display Panel

946 ml NDC: 74793-0008-1